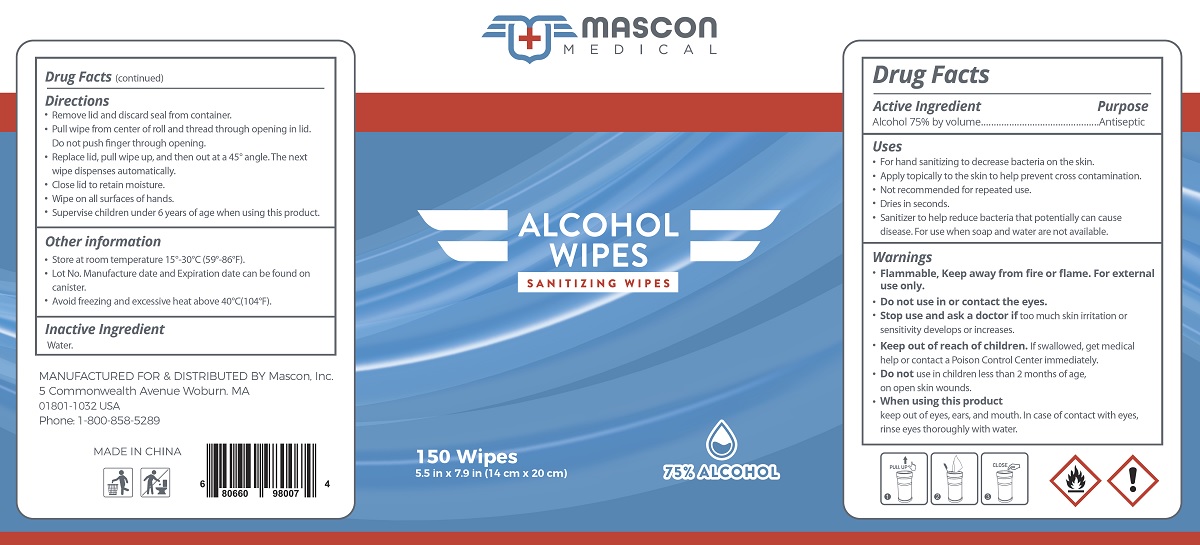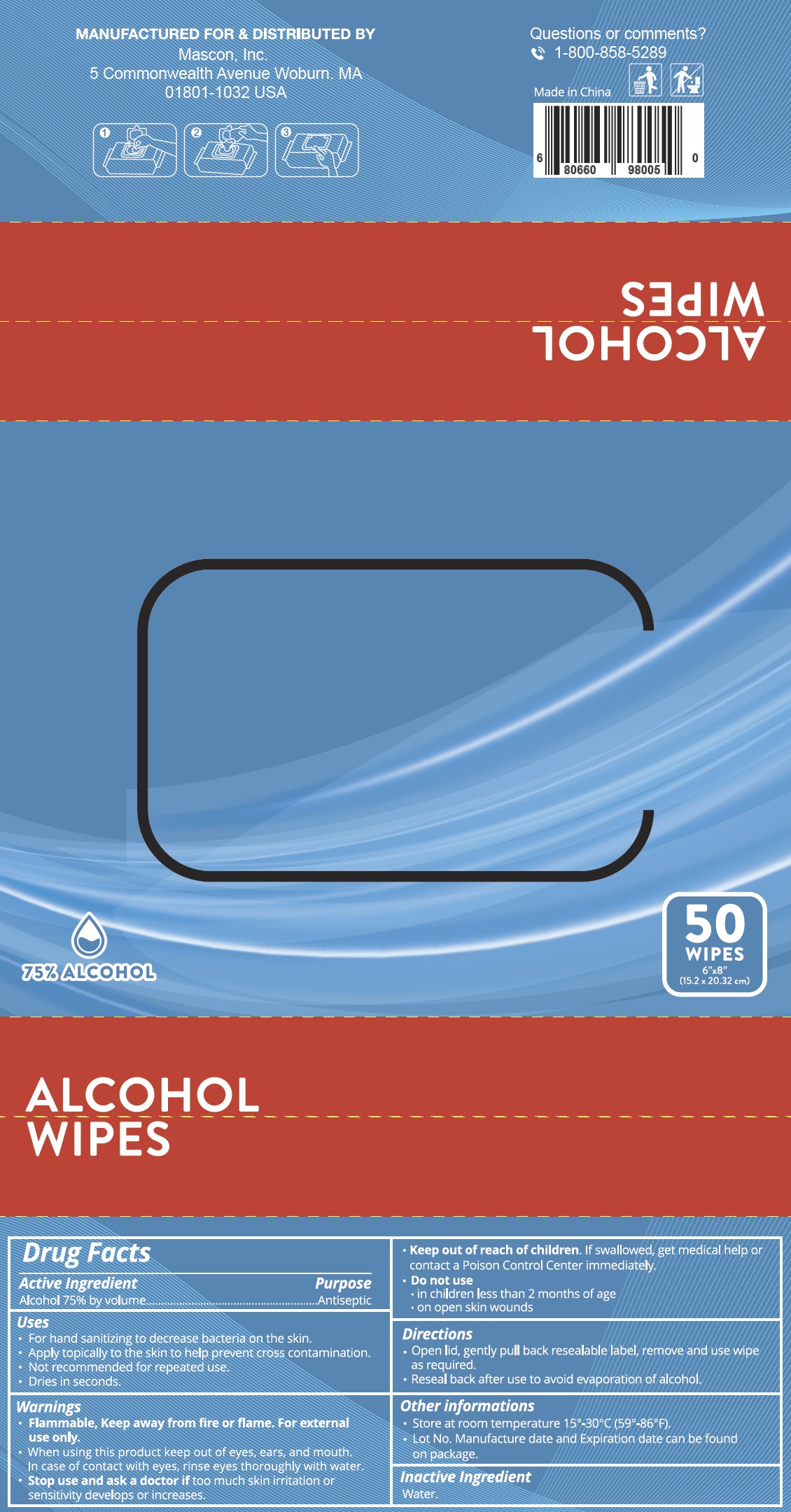 DRUG LABEL: Mascon Medical
NDC: 78593-888 | Form: CLOTH
Manufacturer: Mascon, Inc.
Category: otc | Type: HUMAN OTC DRUG LABEL
Date: 20200702

ACTIVE INGREDIENTS: ALCOHOL 75 mL/100 mL
INACTIVE INGREDIENTS: WATER

Mascon Medical Alcohol Wipes

Active Ingredient

Alcohol 75% by volume

Purpose

Antiseptic

USES

- For hand sanitizing to decrease bacteria on the skin.
- Apply topically to the skin to help prevent cross contamination.
- Not recommended for repeated use.
- Dries in seconds.
- Sanitizer to help reduce bacteria that potentially can cause disease. For use when soap and water are not available.

Warnings

- Flammable, Keep away from fire or flame. For external use only.
- Do not use in or contact the eyes.
- Stop use and ask a doctor if too much skin irritation or sensitivity develops or increases.

- Keep out of reach of children. If swallowed, get medical help or contact a Poison Control Center immediately.

- Do not use in children less than 2 months of age, on open skin wounds.

- When using this product

keep out of eyes, ears, and mouth. In case of contact with eyes, rinse eyes thoroughly with water.

Directions

- Remove lid and discard seal from container.
- Pull wipe from center of roll and thread through opening in lid.
- Do not push finger through opening.
- Replace lid, pull wipe up, and then out at a 45° angle. The next wipe dispenses automatically.
- Close lid to retain moisture.
- Wipe on all surfaces of hands.
- Supervise children under 6 years of age when using this product.

Other information

- Store at room temperature 15°-30°C (59°-86°F).
- Lot No. Manufacture date and Expiration date can be found on canister.
- Avoid freezing and excessive heat above 40°C(104°F).

Inactive Ingredient

Water.

PACKAGE LABEL

Mascon Medical

Alcohol Wipes

Sanitizing Wipes

150 Wipes

5.5 in x 7.9 in (14 cm x 20 cm)

NDC 78593-888-88

50 Wipes

6"x8" (15.2 x 20.32 cm)

NDC 78593-888-08